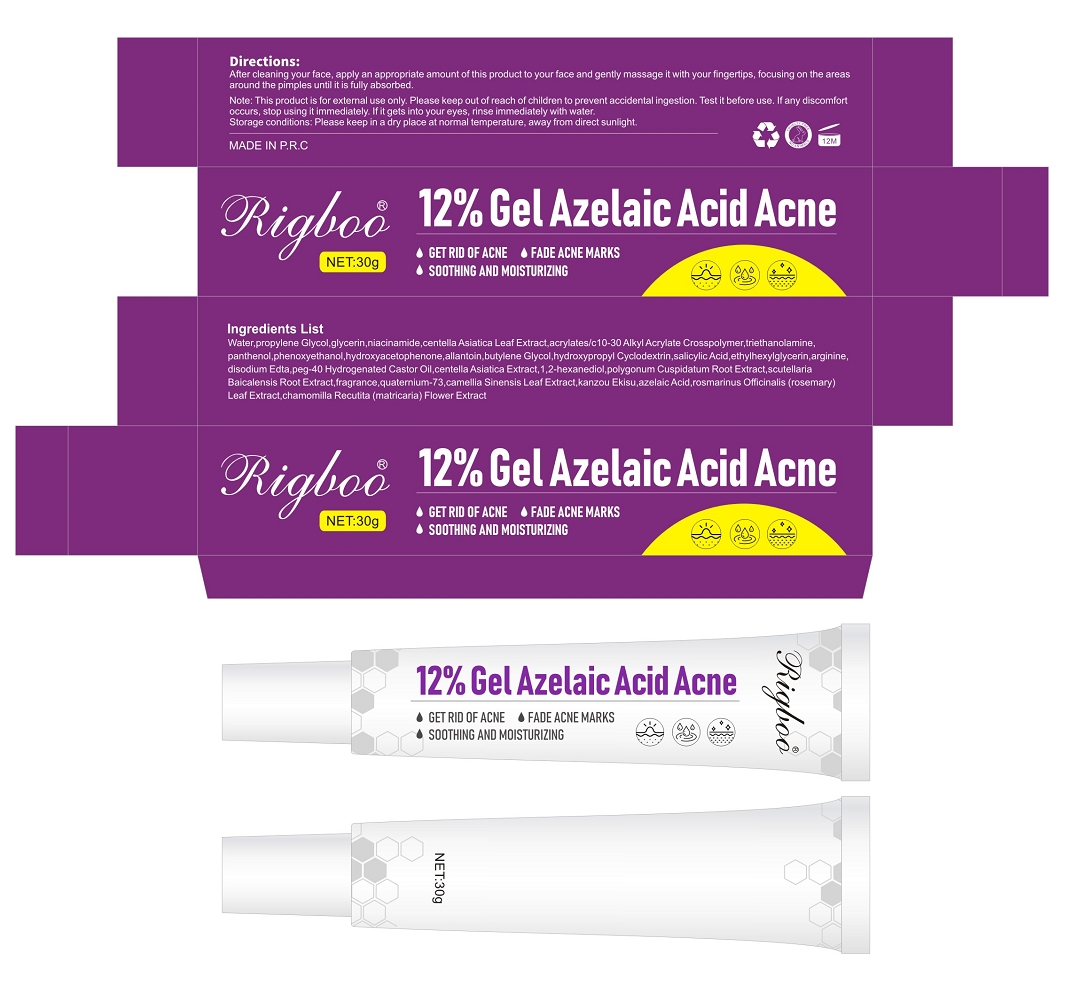 DRUG LABEL: RIGBOO 12% Gel Azelaic Acid Acne
NDC: 84507-045 | Form: GEL
Manufacturer: Guangdong Miaolian Cosmetics Co., Ltd.
Category: otc | Type: HUMAN OTC DRUG LABEL
Date: 20250704

ACTIVE INGREDIENTS: CENTELLA ASIATICA LEAF 0.99 mg/100 g; SALICYLIC ACID 0.07 mg/100 g; AZELAIC ACID 0.002 mg/100 g; QUATERNIUM-73 0.003 mg/100 g
INACTIVE INGREDIENTS: PROPYLENE GLYCOL; CENTELLA ASIATICA; EDETATE DISODIUM; ETHYLHEXYLGLYCERIN; PANTHENOL; MATRICARIA CHAMOMILLA; NIACINAMIDE; PHENOXYETHANOL; CAMELLIA SINENSIS LEAF; WATER; PEG-40 HYDROGENATED CASTOR OIL; 1,2-HEXANEDIOL; TRIETHANOLAMINE; CYCLODEXTRIN; ARGININE; ALLANTOIN; ROSMARINUS OFFICINALIS (ROSEMARY) LEAF OIL; HYDROXYACETOPHENONE; ACRYLATES/C10-30 ALKYL ACRYLATE CROSSPOLYMER (60000 MPA.S); BUTYLENE GLYCOL; SCUTELLARIA BAICALENSIS ROOT; GLYCERIN; POLYGONUM CUSPIDATUM ROOT; GLYCYRRHIZA GLABRA WHOLE; FRAGRANCE MUSKY FLORAL ORC1600904

INDICATIONS AND USAGE

- clean the skin thoroughly before applying this product
- cover the entire affected area with a thin layer one or three times daily

because excessive drying of the skin may occur, start with one application daily, then gradually increase to two or three times daily if needed or as directed by a doctor

- if bothersome dryness or peeling occurs, reduce application to once a day or every other day
- if going outside, apply sunscreen after using this product. If irritation or sensitivity develops, stop use of both products and ask a doctor.

DOSAGE AND ADMINISTRATION

for the treatment of acne

WARNINGS

For external use only

Do not use

if you have very sensitive skin
if you are sensitive to benzoyl peroxide

Stop use and ask a doctor if

irritation becomes severe

KEEP OUT OF REACH OF CHILDREN

If swallowed, get medical help or contact Poison Control Center right away.

ACTIVE INGREDIENT

QUATERNIUM-73 --------0.003%
CENTELLA ASIATICA LEAF EXTRACT --------0.99%
SALICYLIC ACID --------0.07%
AZELAIC ACID --------0.002%

INACTIVE INGREDIENT

WATER
PROPYLENE GLYCOL
GLYCERIN
NIACINAMIDE
HYDROXYACETOPHENONE
1,2-HEXANEDIOL
ACRYLATES/C10-30 ALKYL ACRYLATE CROSSPOLYMER
TRIETHANOLAMINE
PHENOXYETHANOL
ETHYLHEXYLGLYCERIN
PANTHENOL
BUTYLENE GLYCOL
CENTELLA ASIATICA EXTRACT
SCUTELLARIA BAICALENSIS ROOT EXTRACT
POLYGONUM CUSPIDATUM ROOT EXTRACT
CAMELLIA SINENSIS LEAF EXTRACT
KANZOU EKISU
CHAMOMILLA RECUTITA (MATRICARIA) FLOWER EXTRACT
ROSMARINUS OFFICINALIS (ROSEMARY) LEAF EXTRACT
HYDROXYPROPYL CYCLODEXTRIN
ARGININE
ALLANTOIN
DISODIUM EDTA
PEG-40 HYDROGENATED CASTOR OIL
FRAGRANCE

PURPOSE

Evens skin tone & fades spots.
Balances oil & prevents breakouts.